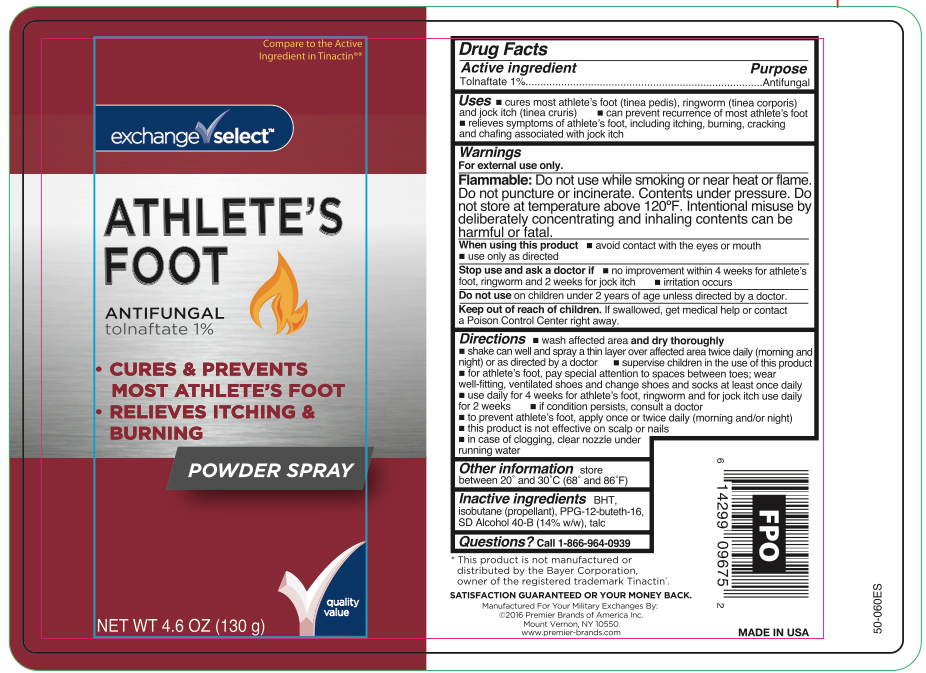 DRUG LABEL: Tolnaftate
NDC: 55301-132 | Form: AEROSOL, SPRAY
Manufacturer: ARMY & AIR FORCE EXCHANGE SERVICE
Category: otc | Type: HUMAN OTC DRUG LABEL
Date: 20251209

ACTIVE INGREDIENTS: TOLNAFTATE 1.3 g/130 g
INACTIVE INGREDIENTS: BUTYLATED HYDROXYTOLUENE; ISOBUTANE; PPG-12-BUTETH-16; ALCOHOL; TALC

Exchange Select Antifungal Tolnaftate Powder Spray

Active ingredient

Tolnaftate 1%

Purpose

Antifungal

Uses

- cures most athlete's foot (tinea pedis), ringworm (tinea corporis) and jock itch (tinea cruris)
- can prevent recurrence of most athlete's foot
- relieves symptoms of athlete's foot, including itching, burning, cracking and chafing associated with jock itch

Warnings

For external use only.

Flammable:

Do not use while smoking or near heat or flame. Do not puncture or incinerate. Contents under pressure. Do not store at temperature above 120°F. Intentional misuse by deliberately concentrating and inhaling contents can be harmful or fatal.

When using this product

- avoid contact with the eyes or mouth
- use only as directed

Stop use and ask a doctor if

- no improvement within 4 weeks for athlete's foot, ringworm and 2 weeks for jock itch
- irritation occurs

Do not use

on children under 2 years of age unless directed by a doctor.

Keep out of reach of children.

If swallowed, get medical help or contact a Poison Control Center right away.

Directions

- wash affected area and dry thoroughly
- shake can well and spray a thin layer over affected area twice daily (morning and

night) or as directed by a doctor

- supervise children in the use of this product
- for athlete's foot, pay special attention to spaces between toes; wear

well-fitting, ventilated shoes and change shoes and socks at least once daily

- use daily for 4 weeks for athlete's foot, ringworm and for jock itch use daily

for 2 weeks

- if condition persists, consult a doctor
- to prevent athlete's foot, apply once or twice daily (morning and/or night)
- this product is not effective on scalp or nails
- in case of clogging, clear nozzle under running water

Other information

store between 20º and 30ºC (68ºF and 86º)

Inactive ingredient

BHT, isobutane (propellant), PPG-12-buteth-16, SD Alcohol 40-B (14% w/w), talc

Questions?

Call 1-866-964-0939

RECENT MAJOR CHANGES

.

Principal Display Panel

exchange select

ATHLETE'S

FOOT

ANTIFUNGAL
tolnaftate 1%

- CURES & PREVENTS
  MOST ATHLETE'S FOOT
- RELIEVES ITCHING &
  BURNING

Powder Spray

NET WT 4.6 OZ (130 g)